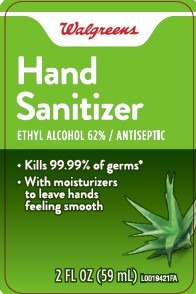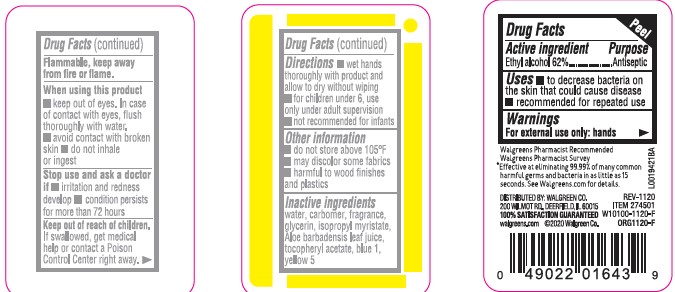 DRUG LABEL: Alcohol
NDC: 0363-0046 | Form: LIQUID
Manufacturer: Walgreen Co.
Category: otc | Type: HUMAN OTC DRUG LABEL
Date: 20260212

ACTIVE INGREDIENTS: ALCOHOL 62 mL/100 mL
INACTIVE INGREDIENTS: CARBOMER INTERPOLYMER TYPE A (ALLYL SUCROSE CROSSLINKED); GLYCERIN; TOCOPHEROL; WATER; ISOPROPYL MYRISTATE; ALOE; FD&C BLUE NO. 1; FD&C YELLOW NO. 5

Walgreens 826.000/826AA rev 1
Moisturizing Hand Sanitizer with Aloe

Active ingredient

Ethyl Alcohol 62%

Purpose

Antiseptic

Uses

- to decrease bacteria on the skin that could cause disease
- recommended for repeated use

Warnings

For external use only: hands

Flammable, keep away from fire or flame

When using this product

- keep out of eyes. In case of contact with eyes, flush thoroughly with water.
- avoid contact with broken skin
- do not inhale of ingest

Stop use and ask a doctor if

- irritation and redness develop
- condition persists for more than 72 hours

Keep out of reach of children.

If swallowed, get medical help or contact a Poison Control Center right away.

Directions

- wet hands thoroughly with product and allow to dry without wiping
- for children under 6, use only under adult supervision
- not recommended for infants

other information

- Do not store above 105° F
- may discolor some fabrics
- harmful to wood finishes and plastics

inactive ingredients

water, carbomer, fragrance, glycerin, isopropyl myristate, Aloe barbadensis leaf juice, tocopheryl acetate, blue 1, yellow 5

ADVERSE REACTION

Walgreens Pharmacist Recommended

Walgreens Pharmacist Survey

*Effective at eliminating 99.99% of many common harmful germs and bacteria in as little as 15 seconds. See Walgreens.com for details.

DISTRIBUTED BY: WALGREEN CO.

200 WILMOT RD., DEERFIELD, IL 60015

100% SATISFACTION GUARANTEED

walgreens.com. ©2020 Walgreen Co.

principal display panel

Walgreens

Hand Sanitizer

ETHYL ALCOHOL 62% / ANTISEPTIC

- Kills 99.99% of germs*
- With moisturizers to leave hands feeling smooth

2 FL OZ (59 mL)